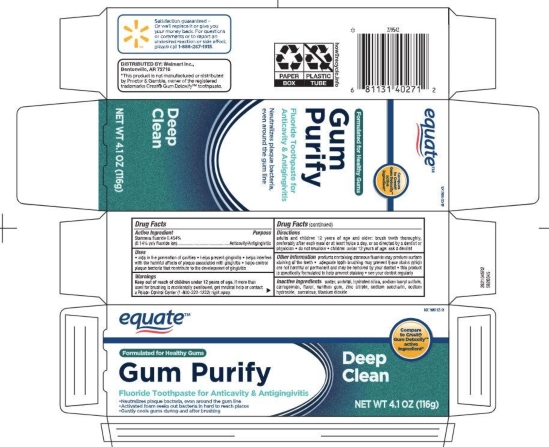 DRUG LABEL: Gum Detoxify
NDC: 79903-025 | Form: PASTE, DENTIFRICE
Manufacturer: Walmart
Category: otc | Type: HUMAN OTC DRUG LABEL
Date: 20250812

ACTIVE INGREDIENTS: STANNOUS FLUORIDE 0.14 g/100 g
INACTIVE INGREDIENTS: ZINC CITRATE; TITANIUM DIOXIDE; SACCHARIN SODIUM; SODIUM HYDROXIDE; SORBITOL; HYDRATED SILICA; XANTHAN GUM; CARRAGEENAN; SODIUM LAURYL SULFATE; SUCRALOSE; WATER

5820045 Equate Gum Care

ACTIVE INGREDIENT

Stannous fluoride 0.454% (0.14% w/v fluoride ion)

PURPOSE

Anticavity/Antigingivitis

INDICATIONS AND USAGE

*aids in the prevention of cavities * helps prevent gingivitis * helps interfere with teh harmful effects of plaque associated with gingivitis * helps control plaque bacteria that contribute to teh development of gingivitis

WARNINGS

Keep out of reach of children under 12 years of age. If more than used for brushing is accidentally swallowed, get medical help or contact a Poison Control Center (1-800-222-1222) right away.

DOSAGE AND ADMINISTRATION

adults and children 12 years of age and older: brush teeth thoroughly, preferably after each meal or at least twice a day, or as directed by a dentist or physician * do not swallow * children under 12 years of age: ask a dentist

OTHER SAFETY INFORMATION

products containing stannous fluoride may produce surface staining of the teeth * adequate tooth brushing may prevent these stains which are not harmful or permanent adn may be removed by your dentist * this product is specifically formulated to help prevent staining * see your dentist regularly

INACTIVE INGREDIENT

water, sorbitol, hydrated silica, sodium lauryl sulfate, carrageenan, flavor, xanthan gum, zinc citrate, sodium saccharin, sodium hydroxide, sucralose, titanium dioxide